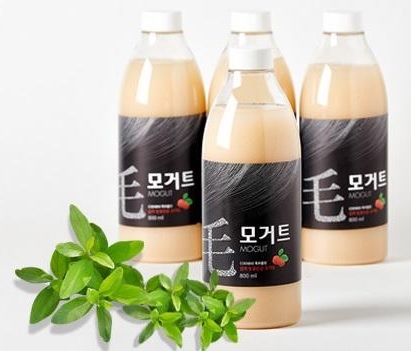 DRUG LABEL: MOGUT
NDC: 71682-0001 | Form: LIQUID
Manufacturer: COENBIO CO., LTD.
Category: otc | Type: HUMAN OTC DRUG LABEL
Date: 20200112

ACTIVE INGREDIENTS: LACTOBACILLUS REUTERI 20 g/100 mL; ENTEROCOCCUS FAECIUM 20 g/100 mL
INACTIVE INGREDIENTS: PERSIMMON

Drug Facts

ACTIVE INGREDIENT

Lactobacillus and Leuconostocspp. from Korean Kimchi and soybean paste

INACTIVE INGREDIENT

Persimmon vinegar(0.1%),Black soybean(0.1%), Dried broccoli sprout(0.1%), Mixed probioticsfermented liquid(99.7%)

PURPOSE

•Cure chronic constipation
•Diet effect
•Alleviation of lactose intolerance, diarrhea, and peptic ulcer
•Anti-allergic effects

•Stimulation of hair growth: pilatoryeffect
•Degradation of cholesterol and neutral lipid in blood vessel
•Anti-oxidant effect

keep out of reach of the children

INDICATIONS AND USAGE

-Drinktwice a day (50ml per each time)
-Recommending drink it in the morning and night.
-It is okay to drink after eating if the person is sensible for their stomach.

WARNINGS

-Keep it in the refrigerator(4~7°C). DO NOT KEEP IT IN THE FREEZER
-Under above condition 3 months in the refrigerator but recommendtodrink it within 1 month for better taste and flavor.

DOSAGE AND ADMINISTRATION

-Drinktwice a day (50ml per each time)
-Recommending drink it in the morning and night.
-It is okay to drink after eating if the person is sensible for their stomach.